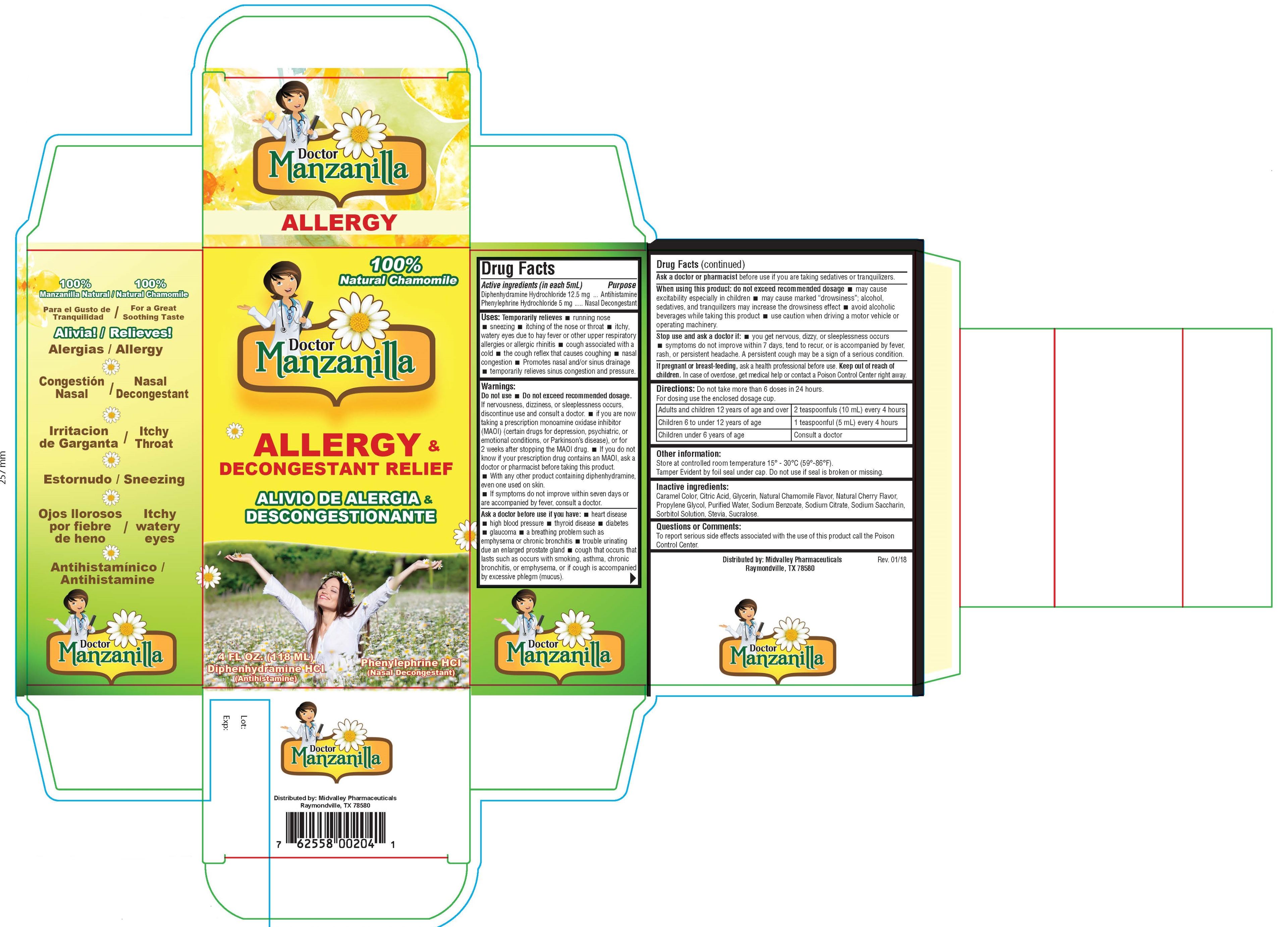 DRUG LABEL: DOCTOR MANZANILLA ALLERGY AND DECONGESTANT RELIEF
NDC: 62558-002 | Form: SYRUP
Manufacturer: Mid Valley Pharmaceuticals LLC
Category: otc | Type: HUMAN OTC DRUG LABEL
Date: 20200430

ACTIVE INGREDIENTS: DIPHENHYDRAMINE HYDROCHLORIDE 12.5 mg/5 mL; PHENYLEPHRINE HYDROCHLORIDE 5 mg/5 mL
INACTIVE INGREDIENTS: SODIUM CITRATE; CHAMOMILE; SACCHARIN SODIUM; ANHYDROUS CITRIC ACID; STEVIA LEAF; GLYCERIN; PROPYLENE GLYCOL; WATER; SODIUM BENZOATE; SORBITOL SOLUTION; SUCRALOSE

DRUG LABEL

DRUG FACTS:

ACTIVE INGREDIENTS (IN EACH 5ML)

Diphenhydramine Hydrochloride 12.5mg

Phenylephrine Hydrochloride 5mL

PURPOSE:

Antihistamine

Nasal Decongestant

USES:

Temporarily relieves:

- runny nose
- sneezing
- itching of the nose or throat
- itchy, watery eyes due to hay fever or other upper respiratory allergies or allergic rhinitis
- cough associated with a cold
- the cough reflex that causes coughing
- nasal congestion
- Promotes nasal and/or sinus drainage
- temporarily relieves sinus congestion and pressure.

WARNINGS:

Do not use - Do not exceed recommended dosage.

- If nervousness, dizziness, or sleeplessness occurs, discontinue use and consult a doctor.
- If you are now taking a prescription monoamine oxidase inhibitor (MAOI) (certain drugs for depression, psychiatric, or emotional conditions, or Parkinson's disease), or for 2 weeks after stopping the MAOI drug.
- If you do not know if your prescription drug contains an MAOI, ask a doctor or pharmacist before taking this product.
- With any other product containing diphenhydramine, even one used on skin. If symptoms do not improve within seven days or are accompanied by fever, consult a doctor.

Ask a doctor before use if you have:

- heart disease
- high blood pressure
- thyroid disease
- diabetes
- glaucoma
- a breathing problem such as emphysema or chronic bronchitis
- trouble urinating due an enlarged prostate gland
- cough that occurs that lasts such as occurs with smoking, asthma, chronic bronchitis, or emphysema, or if cough is accompanied by excessive phlegm (mucus).

Ask a doctor or pharmacist

before use if you are taking sedatives or tranquilizers.

When using this product:

- do not exceed recommended dosage
- may cause excitability especially in children
- may cause marked drowsiness; alcohol, sedatives, and tranquilizers may increase the drowsiness effect
- avoid alcoholic beverages while taking this product
- use caution when driving a motor vehicle or operating machinery.

Stop use and ask a doctor if:

- you get nervous, dizzy, or sleeplessness occurs
- symptoms do not improve within 7 days, tend to recur, or is accompanied by fever, rash, or persistent headache. A persistent cough may be a sign of a serious condition.

If pregnant or breast-feeding,

ask a health professional before use.

Keep out of reach of children.

In case of overdose, get medical help or contact a Poison Control Center right away.

DIRECTIONS:

Do not take more than 6 doses in 24 hours.

Adults and children 12 years of age and over | 2 teaspoonfuls (10mL) every 4 hours
Children 6 to under 12 years of age | 1 teaspoonfuls (5mL) every 4 hours
Children under 6 years of age | Consult a doctor

OTHER INFORMATION:

Store at controlled room temperature 15º - 30ºC (59º-86ºF). Each dose contains less than 5 mg sodium.

INACTIVE INGREDIENTS:

Caramel Color, Citric Acid, Glycerin, Natural Chamomile, Natural Cherry Flavor, Propylene Glycol, Purified Water, Sorbitol, Sodium Benzoate, Sodium Citrate, Sodium Saccharin, Stevia, Sucralose.

ADVERSE REACTIONS:

In case of overdose, get medical help or contact a Poison Control Center right away.

Doctor Manzanilla Allergy Carton Label

Doctor Manzanilla Allergy and Decongestant Carton

Doctor Manzanilla

ALLERGY

100% Natural Chamomile

Doctor Manzanilla

ALLERGY &

DECONGESTANT RELIEF

4 FL OZ. (118 ml)

Diphenhydramine HCl

(Antihistamine)

Phenylephrine HCl

(Nasal Decongestant)

100% Manzanilla Natural

Congestion Nasal

Doctor Manzanilla

100% Natural Chamomile

FOR A GREAT SOOTHING TASTE

Relieves!

Allergy

Nasal Decongestant

Itchy Throat

Sneezing

Itching watery eyes

Antihistamine

Doctor Manzanilla

Distributed by: Midvalley Pharmaceuticals
Raymondville, TX 78580